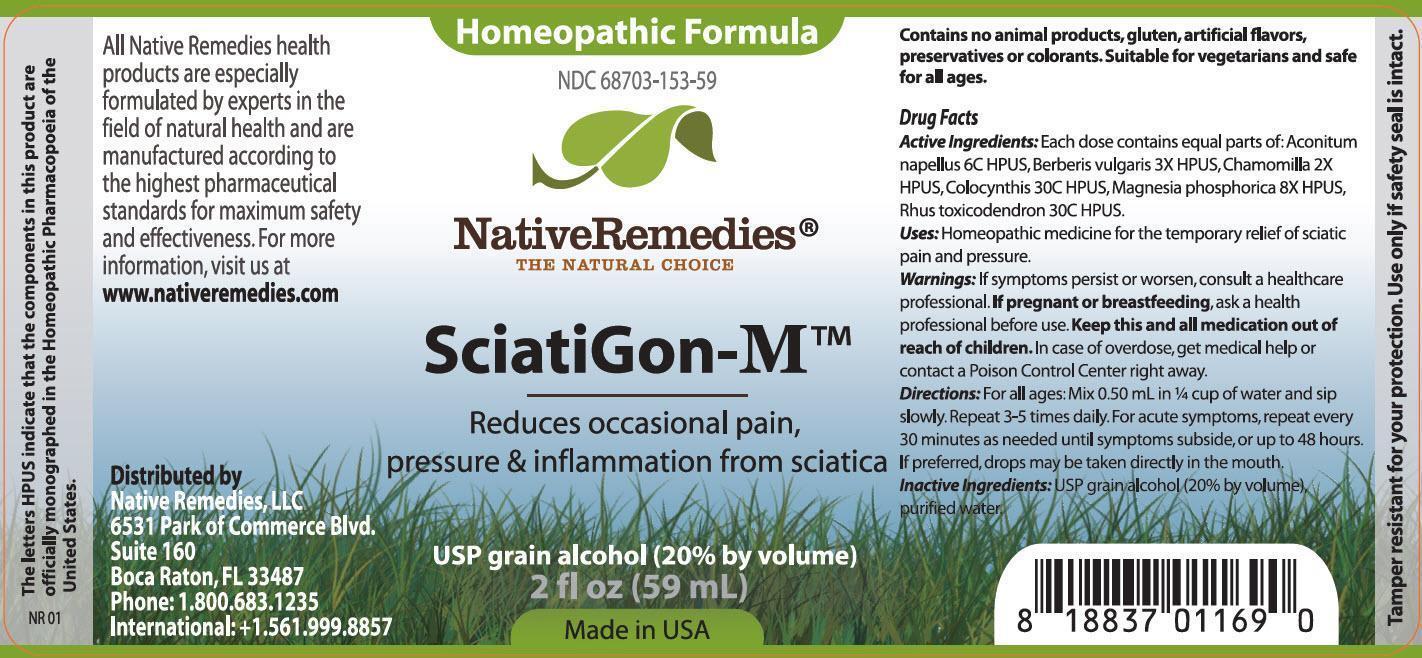 DRUG LABEL: SciatiGon-M
NDC: 68703-153 | Form: TINCTURE
Manufacturer: Native Remedies, LLC
Category: homeopathic | Type: HUMAN OTC DRUG LABEL
Date: 20141207

ACTIVE INGREDIENTS: ACONITUM NAPELLUS 6 [hp_C]/1 mL; BERBERIS VULGARIS ROOT BARK 3 [hp_X]/1 mL; MATRICARIA RECUTITA 2 [hp_X]/1 mL; CITRULLUS COLOCYNTHIS FRUIT PULP 30 [hp_C]/1 mL; MAGNESIUM PHOSPHATE, DIBASIC TRIHYDRATE 8 [hp_X]/1 mL; TOXICODENDRON PUBESCENS LEAF  30 [hp_C]/1 mL
INACTIVE INGREDIENTS: ALCOHOL; WATER

SciatiGon-M

PURPOSE

Reduces occasional pain, pressure and inflammation from sciatica

Drug Facts
Active Ingredients: Each dose contains equal parts of: Aconitum napellus 6C HPUS, Berberis vulgaris 3X HPUS, Chamomilla 2 X HPUS, Colocynthis 30C HPUS, Magnesia phosphorica 8X HPUS, Rhus toxicodendron 30C HPUS

INDICATIONS AND USAGE

Uses:Homeopathic medicine for temporary relief of sciatic pain and pressure

WARNINGS

Warnings: If symptoms persist or worsen, consult a healthcare professional

PREGNANCY OR BREAST FEEDING

If pregnant or breastfeeding, ask a health professional before use

KEEP OUT OF REACH OF CHILDREN

Keep this and all medication out of reach of children

OVERDOSAGE

In case of overdose, get medical help or contact a Poison Control Center right away

DOSAGE AND ADMINISTRATION

Directions:For all ages: Mix 0.50 mL in 1/4 cup of water and sip slowly. Repeat 3-5 times daily. For acute symptoms, repeat every 30 minutes as needed until symptoms subside, or up to 48 hours. If preferred, drops may be taken directly in the mounth

INACTIVE INGREDIENT

Inactive Ingredients: USP grain alcohol (20% by volume), purified water

PATIENT COUNSELING INFORMATION

The letters HPUS indicate that the components in this product are officially monographed in the Homeopathic Pharmacopoeia of the United States.

All Native Remedies health products are especially formulated by experts in the field of natural health and are manufactured according to the highest pharmaceutical standards for maximum safety and effectiveness. For more information, visit us at www.nativeremedies.com

Distributed by
Native Remedies, LLC
6531 Park of Commerce Blvd.
Suite 160
Boca Raton, FL 33487
Phone: 1.800.683.1235
International: +1.561.999.8857

Contains no animal products, gluten, artificial flavors, preservatives or colorants. Suitable for vegetarians and safe for all ages.

STORAGE AND HANDLING

Tamper resistant for your protection. Use only if safety seal is intact